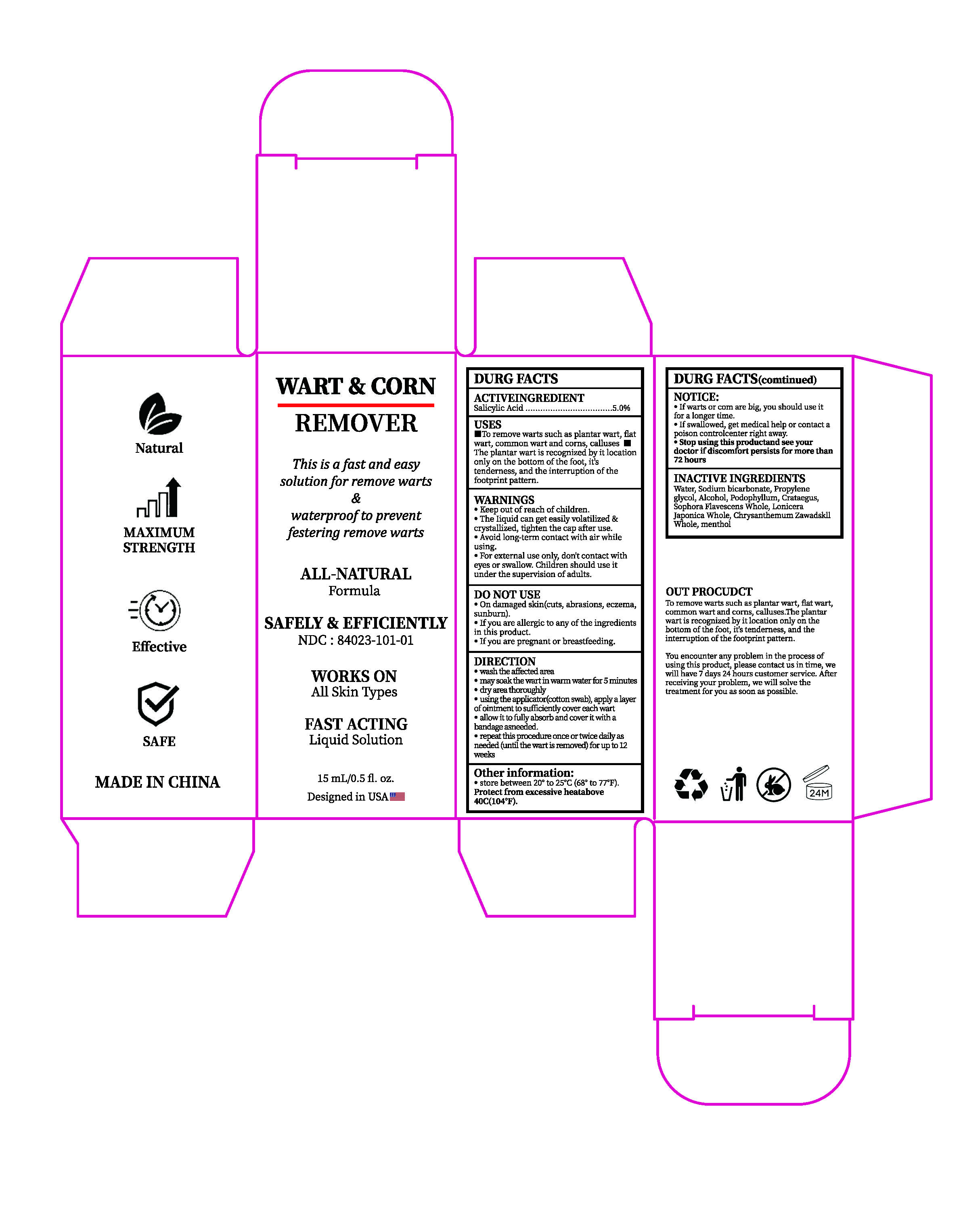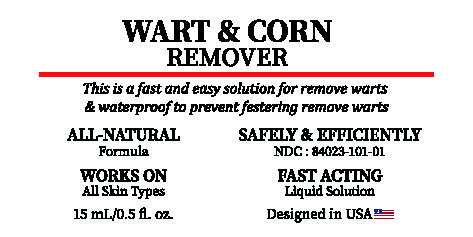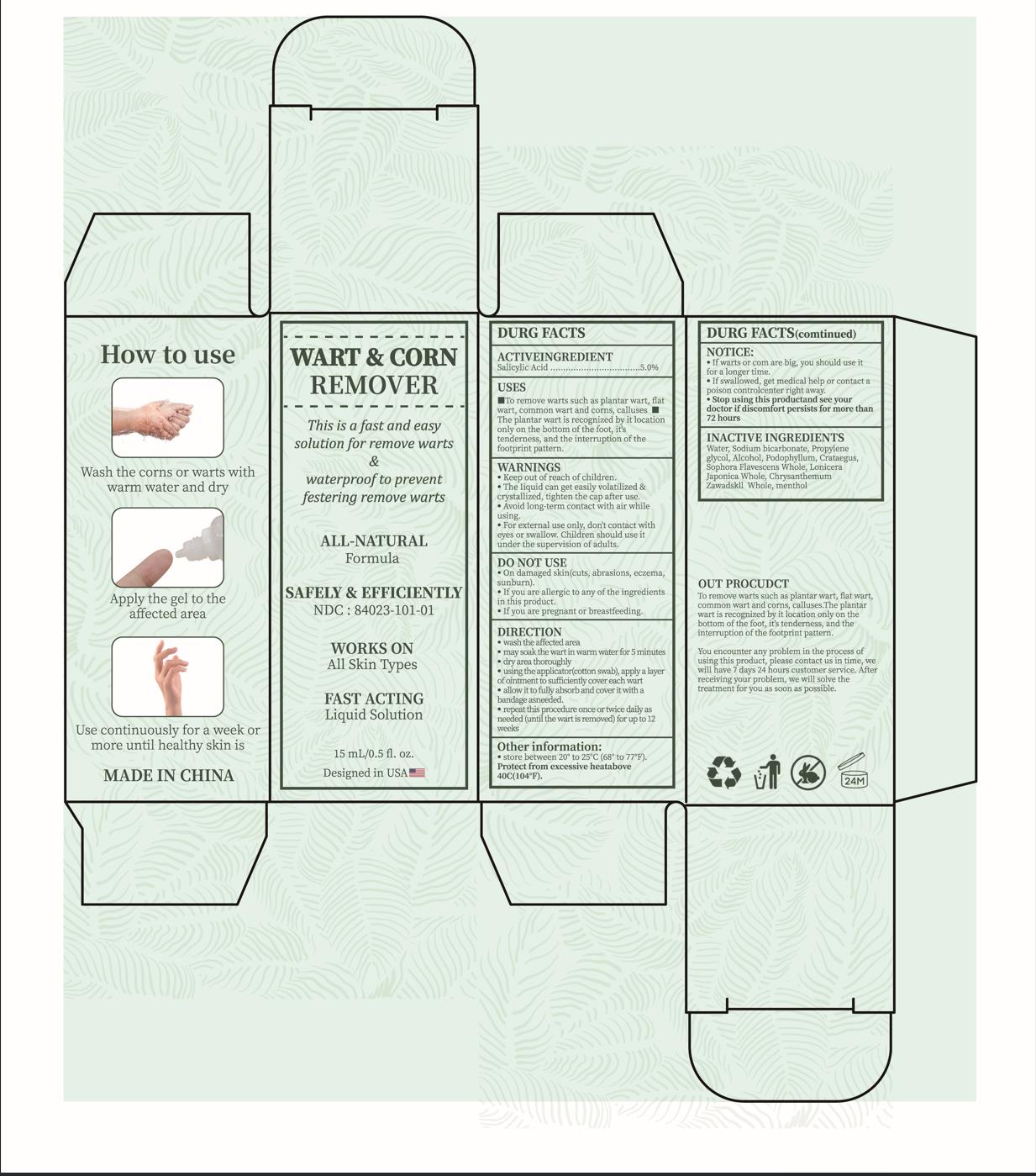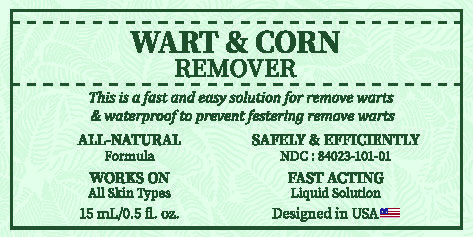 DRUG LABEL: WART CORN REMOVER
NDC: 84023-101 | Form: LIQUID
Manufacturer: Shenzhen Yangan Technology Co., Ltd.
Category: otc | Type: HUMAN OTC DRUG LABEL
Date: 20240308

ACTIVE INGREDIENTS: SALICYLIC ACID 5 g/100 mL
INACTIVE INGREDIENTS: WATER; MENTHOL; CHRYSANTHEMUM ZAWADSKII WHOLE; LONICERA JAPONICA WHOLE; SOPHORA FLAVESCENS WHOLE; HAWTHORN LEAF WITH FLOWER; PODOPHYLLUM; ALCOHOL; PROPYLENE GLYCOL; SODIUM BICARBONATE

WART & CORN REMOVER

WART & CORN REMOVER

ACTIVE INGREDIENT

Salicylic acid 5%

PURPOSE

REMOVES SKIN TAGS

INDICATIONS AND USAGE

Uses for the removal of common warts.The common wart is easily recognized by the rough cauliflower likeappearance of the surface.
The plantar wart is recognized by it slocation only on the bottom of the foot, its tenderness,and the interruption of the footprint pattern.
for removal of plantar warts on the bottom of the foot.

Keep out of reach of children.
The liquid can get easily volatilized & crystallized, tighten the cap after use.
Avoid long-term contact with air while using.
For external use only dont contact with eyes or swallow Children should use it under the supervision of adults.

DO NOT USE

On damaged skin(cuts, abrasions, eczema sunburn).
On irritatedinfected or reddened skin.
If you are a diabetic or if you have poor blood circulation.
If you are pregnant or breastfeeding.

WHEN USING

wash the affected area.
may soak the wart in warmn water for 5 minutes.
dry area thoroughly.
using the applicator(cotton swab), apply a layer of ointment to sufficiently cover each wart.
allow it to fully absorb and cover it with a bandage asneeded.
repeat this procedure once or twice dailyas needed (until the wartis removed) for up to 12 weeks.

STOP USE

Stop using this productand see your doctor if discomfort persists for more than 72 hours

Keep out of reach of children.

DOSAGE AND ADMINISTRATION

using the applicator(cotton swab), apply a layer of ointment to sufficiently cover each wart.
allow it to fully absorb and cover it with a bandage asneeded.
repeat this procedure once or twice daily as needed (until the wartis removed) for up to 12 weeks.

STORAGE AND HANDLING

store between 20° to 25°C (68° to 77°F).
Protect from excessive heatabove 40C(104°F).

INACTIVE INGREDIENT

Water,Sodiumbicarbonate,Pmpylene glycol,Alcohol,Podophyllum,Crataegus, SophoraFlavescensWhole,Lonicera Japonica Whole, Chrysanthemum Zawadslill Whole,menthol